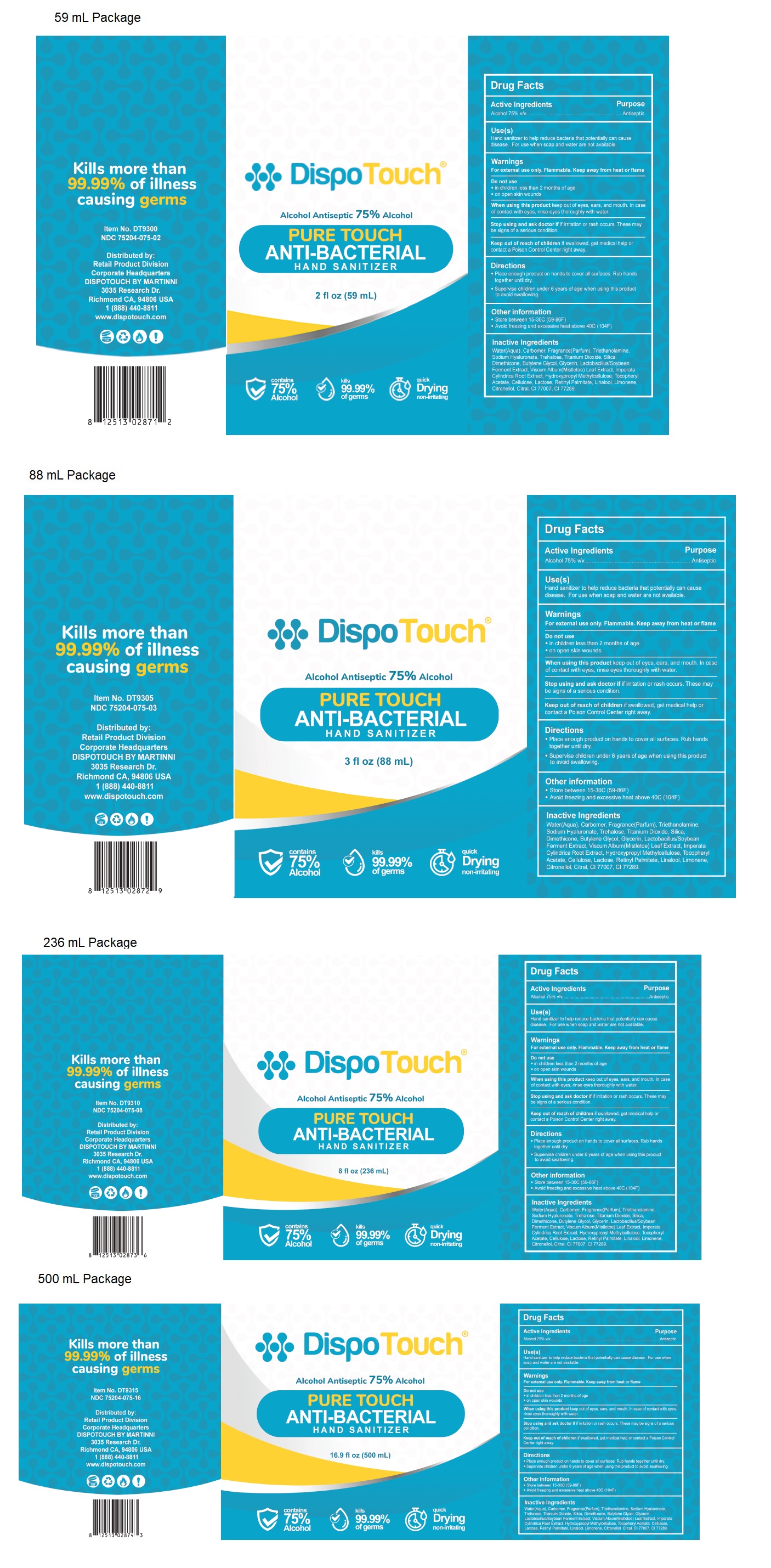 DRUG LABEL: DispoTouch
NDC: 75204-075 | Form: GEL
Manufacturer: Martinni Beauty Inc
Category: otc | Type: HUMAN OTC DRUG LABEL
Date: 20231220

ACTIVE INGREDIENTS: ALCOHOL 75 mL/100 mL
INACTIVE INGREDIENTS: WATER; HYPROMELLOSE, UNSPECIFIED; .ALPHA.-TOCOPHEROL ACETATE; POWDERED CELLULOSE; LACTOSE, UNSPECIFIED FORM; VITAMIN A PALMITATE; LINALOOL, (+/-)-; LIMONENE, (+)-; .BETA.-CITRONELLOL, (R)-; CITRAL; ULTRAMARINE BLUE; CHROMIUM HYDROXIDE GREEN; CARBOMER HOMOPOLYMER, UNSPECIFIED TYPE; TROLAMINE; HYALURONATE SODIUM; TREHALOSE; TITANIUM DIOXIDE; SILICON DIOXIDE; DIMETHICONE; BUTYLENE GLYCOL; GLYCERIN; SOYBEAN; VISCUM ALBUM FRUITING TOP; IMPERATA CYLINDRICA ROOT

DispoTouch® ANTI-BACTERIALHAND SANITIZER

Active Ingredients

Alcohol 75% v/v

Purpose

Antiseptic

Use(s)

Hand sanitizer to help reduce bacteria that potentially can cause disease. For use when soap and water are not available.

Warnings

For external use only. Flammable. Keep away from heat or flame

Do not use

• in children less than 2 months of age

• on open skin wounds

When using this productkeep out of eyes, ears, and mouth. In case of contact with eyes, rinse eyes thoroughly with water.

Stop using and ask doctor ifirritation or rash occurs. These may be signs of a serious condition.

KEEP OUT OF REACH OF CHILDREN

Keep out of reach of childrenif swallowed, get medical help or contact a Poison Control Center right away.

Directions

• Place enough product on hands to cover all surfaces. Rub hands together until dry.

• Supervise children under 6 years of age when using this product to avoid swallowing.

Other information

• Store between 15-30°C (59-86°F)

• Avoid freezing and excessive heat above 40°C (104°F)

Inactive Ingredients

Water (Aqua), Carbomer, Fragrance(Parfum), Triethanolamine, Sodium Hyaluronate, Trehalose, Titanium Dioxide, Silica, Dimethicone, Butylene Glycol, Glycerin, Lactobacillus/Soybean Ferment Extract, Viscum Album (Mistletoe) Leaf Extract, Imperata Cylindrica Root Extract, Hydroxypropyl Methylcellulose, Tocopheryl Acetate, Cellulose, Lactose, Retinyl Palmitate, Linalool, Limonene, Citronellol, Citral, CI 77007, CI 77289.

Alcohol Antiseptic 75% Alcohol

PURE TOUCH

contains 75% Alcohol

kills 99.99% of germs

quick Dryingnon-irritating

Kills more than 99.99% of illness causing germs

Item No. DT9300

Distributed by:

Retail Product Division

Corporate Headquarters

DISPOTOUCH BY MARTINNI

3035 Research Dr.

Richmond CA, 94806 USA

1 (888) 440-8811

www.dispotouch.com